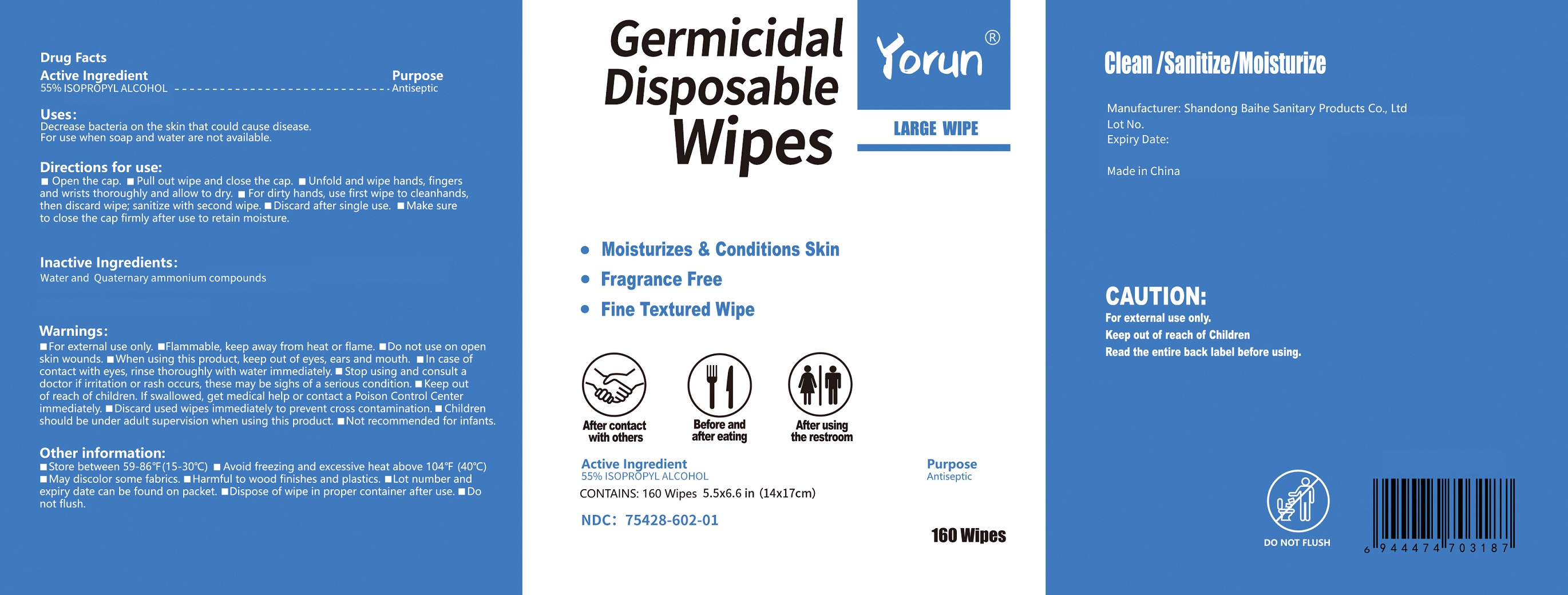 DRUG LABEL: YORUN Germicidal Disposable Wipes
NDC: 75428-602 | Form: CLOTH
Manufacturer: Shandong BaiHe Sanitary Products Co., Ltd.
Category: otc | Type: HUMAN OTC DRUG LABEL
Date: 20201024

ACTIVE INGREDIENTS: ISOPROPYL ALCOHOL 55 1/100 1
INACTIVE INGREDIENTS: N-ALKYL DIMETHYL BENZYL AMMONIUM CHLORIDE (C12-C18); WATER

YORUN Germicidal Disposable Wipes

Active Ingredient

ISOPROPYL ALCOHOL 55%

Purpose

Antiseptic

Uses

Decrease bacteria on the skin that could cause disease

For use when soap and water are not available

Warnings

For external use only. Flammable, keep away from heat or flame.

Do not use

- on open skin wounds

When using this product, keep out of eyes, ears and mouth. In case of contact with eyes, rinse thoroughly with water immediately. If swallowed, get medical help or contact a Poison Control Center immediately. Discard used wipes immediately to prevent cross contamination. Children should be under adult supervision when using this product.

STOP USE

Stop using and consult a doctor if irritation or rash occurs, these may be sighs of a serious condition.

Keep out of reach of children. Not recommended for infants.

Directions for use

- Open the cap. Pull out wipe and close the cap. Unfold and wipe hands, fingers and wrists thoroughly and allow to dry. For dirty hands, use first wipe to clean hands then discard wipe; sanitize with second wipe. Discard after single use. Make sure to close the cap firmly after use to retain moisture.

Other information

- Store between 59-86°F (15-30°C). Avoid freezing and excessive heat above 104°F (40°C). May discolor some fabrics. Harmful to wood finishes and plastics. Lot number and expiry date can be found on label. Dispose of wipe in proper container after use. Do not flush.

Inactive ingredients

PURE WATER and QUATERNARY AMMONIUM COMPOUNDS